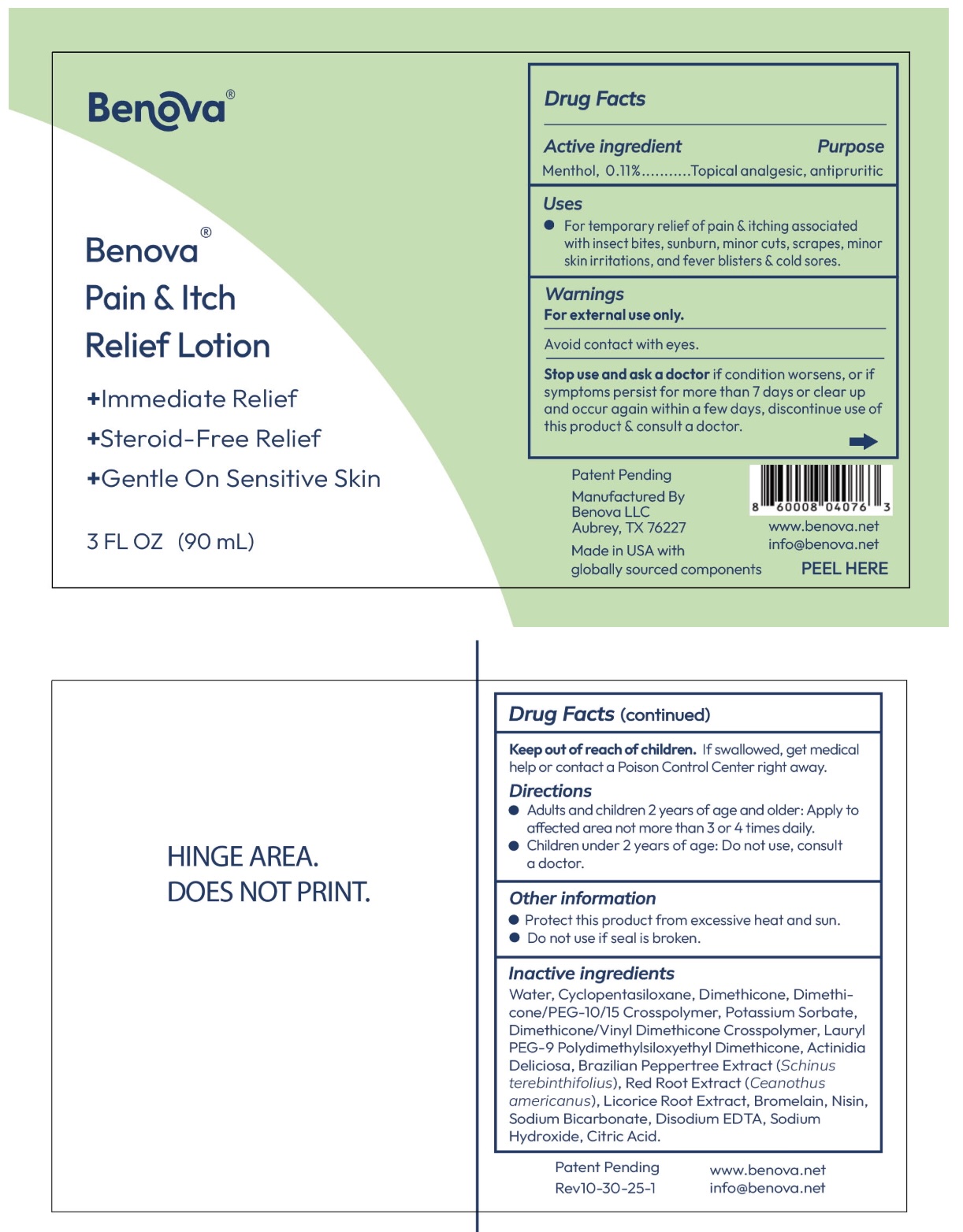 DRUG LABEL: BENOVA PAIN AND ITCH RELIEF
NDC: 87150-001 | Form: LOTION
Manufacturer: BENOVA RX LLC
Category: otc | Type: HUMAN OTC DRUG LABEL
Date: 20251029

ACTIVE INGREDIENTS: MENTHOL 1.1 mg/1 mL
INACTIVE INGREDIENTS: POTASSIUM SORBATE; DIMETHICONE/VINYL DIMETHICONE CROSSPOLYMER (SOFT PARTICLE); BRAZILIAN PEPPER; SODIUM BICARBONATE; EDETATE DISODIUM; DIMETHICONE/PEG-10/15 CROSSPOLYMER; WATER; SODIUM HYDROXIDE; ACTINIDIA DELICIOSA (KIWI) FRUIT; CEANOTHUS AMERICANUS LEAF; DIMETHICONE; LAURYL PEG-9 POLYDIMETHYLSILOXYETHYL DIMETHICONE; CITRIC ACID; LICORICE; BROMELAIN; NISIN; CYCLOPENTASILOXANE

Active ingredient Purpose

Menthol, 0.11%...........Topical analgesic, antipruritic

Uses

For temporary relief of pain & itching associated with insect bites, sunburn, minor cuts, scrapes, minor skin irritations, and fever blisters & cold sores.

Warnings

For external use only.

Avoid contact with eyes.

Stop use and ask a doctor if condition worsens, or if symptoms persist for more than 7 days or clear up and occur again within a few days, discontinue use of this product & consult a doctor.

Directions

Adults and children 2 years of age and older: Apply to affected area not more than 3 or 4 times daily. Children under 2 years of age: Do not use, consult
a doctor.

Other information

Protect this product from excessive heat and sun.

Do not use if seal is broken.

Inactive ingredients

Water, Cyclopentasiloxane, Dimethicone, Dimethi- cone/PEG-10/15 Crosspolymer, Potassium Sorbate, Dimethicone/Vinyl Dimethicone Crosspolymer, Lauryl PEG-9 Polydimethylsiloxyethyl Dimethicone, Actinidia Deliciosa, Brazilian Peppertree Extract (Schinus terebinthifolius), Red Root Extract (Ceanothus americanus), Licorice Root Extract, Bromelain, Nisin, Sodium Bicarbonate, Disodium EDTA, Sodium Hydroxide, Citric Acid.

Warnings

For external use only.

Avoid contact with eyes.

Stop use and ask a doctor if condition worsens, or if symptoms persist for more than 7 days or clear up and occur again within a few days, discontinue use of this product & consult a doctor.

Keep out of reach of children. If swallowed,get medical help or contact a Poison Control Center right away.

Directions

Adults and children 2 years of age and older: Apply to affected area not more than 3 or 4 times daily. Children under 2 years of age: Do not use, consult a doctor.

Keep out of reach of children. If swallowed, get medical help or contact a Poison Control Center immediately.

PACKAGE LABEL

Benova®
Pain & Itch
Relief Lotion
+Immediate Relief
+Steroid-Free Relief
+Gentle On Sensitive Skin
3 FL OZ (90 mL)

See uploaded image Benova_PainItchReliefLotion_3floz_PeelBack_FullLabel.jpg.